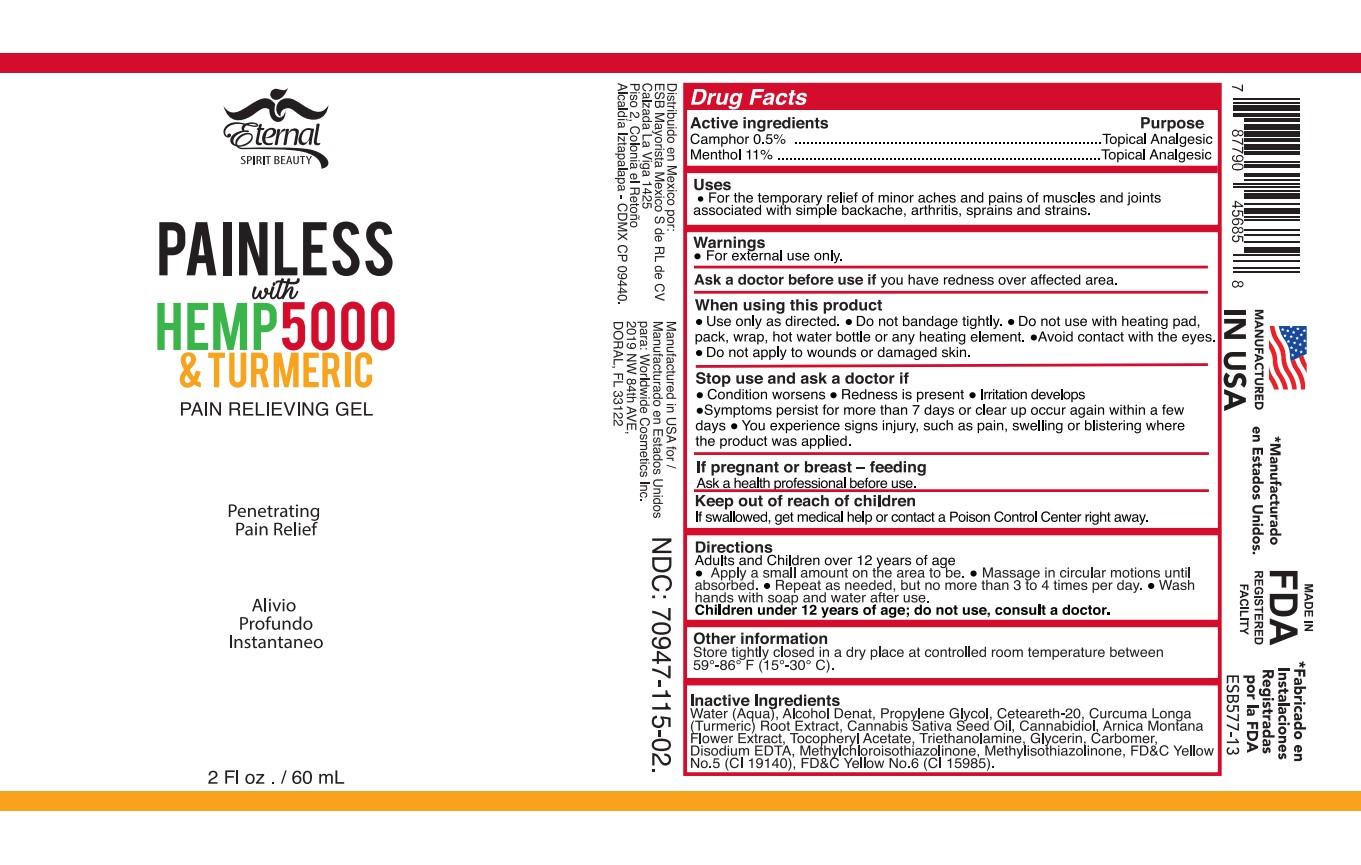 DRUG LABEL: ETERNAL SPIRIT BEAUTY PAINLESS
NDC: 70947-115 | Form: GEL
Manufacturer: Worldwide Cosmetics, Inc
Category: otc | Type: HUMAN OTC DRUG LABEL
Date: 20240226

ACTIVE INGREDIENTS: MENTHOL, UNSPECIFIED FORM 11 g/100 mL; CAMPHOR (SYNTHETIC) 0.5 g/100 mL
INACTIVE INGREDIENTS: METHYLISOTHIAZOLINONE; METHYLCHLOROISOTHIAZOLINONE; CANNABIS SATIVA SEED OIL; FD&C YELLOW NO. 5; GLYCERIN; TURMERIC; ARNICA MONTANA FLOWER; FD&C YELLOW NO. 6; ALCOHOL; .ALPHA.-TOCOPHEROL ACETATE; POLYOXYL 20 CETOSTEARYL ETHER; WATER; PROPYLENE GLYCOL; CANNABIDIOL; TROLAMINE; CARBOMER 940; EDETATE DISODIUM

70947-115-02

ACTIVE INGREDIENT

Camphor 0.5%

Menthol 11%

PURPOSE

Topical Analgesic

USE

For the temporary relief of minor aches and pains of muscles and joints associated
with simple backache, arthritis, sprains and strains.

WARNINGS

For external use only.

Ask a doctor before use if you have redness over affected area.

WHEN USING

Use only as directed.
Do not bandage tightly.
Do not use with heating pad, pack, wrap, hot water bottle or any heating element.
Avoid contact with the eyes.

Do not apply to wounds or damaged skin.

Stop use and ask a doctor if

Condition worsens.
Redness is present.
Irritation develops.
Symptoms persist for more than 7 days or clear up occur again within a few days.

You experience signs injury, such as pain, swelling or blistering where the product was applied.

If pregnant or breast – feeding

Ask a health professional before use.

KEEP OUT OF REACH OF CHILDREN

If swallowed, get medical help, or contact a Poison Control Center right away.

DIRECTIONS

Adults and Children over 12 years

Apply a small amount on the area to be.
Massage in circular motions until absorbed.
Repeat as needed, but no more than 3 to 4 times per day.
Wash hands with soap and water after use.

Children under 12 years of age: do not use, consult a doctor.

OTHER INFORMATION

Store at room temperature 15° - 30°C (59° - 86°F)

INACTIVE INGREDIENT

Water (Aqua), Alcohol Denat, Propylene Glycol, Ceteareth-20, Curcuma Longa (Turmeric) Root Extract, Cannabis Sativa Seed Oil, Cannabidiol, Arnica Montana Flower Extract, Tocopheryl Acetate, Triethanolamine, Glycerin, Carbomer, Disodium EDTA, Methylchloroisothiazolinone, Methylisothiazolinone, FD&C Yellow No.5 (CI 19140), FD&C Yellow No.6 (CI 15985).